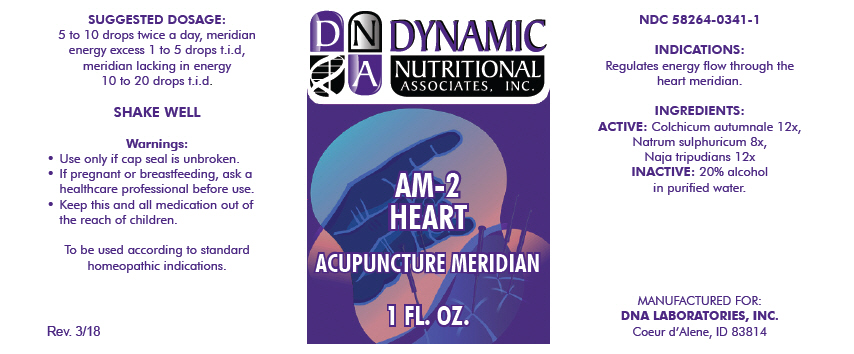 DRUG LABEL: AM-2
NDC: 58264-0341 | Form: SOLUTION
Manufacturer: DNA Labs, Inc.
Category: homeopathic | Type: HUMAN OTC DRUG LABEL
Date: 20250109

ACTIVE INGREDIENTS: COLCHICUM AUTUMNALE WHOLE 12 [hp_X]/1 mL; SODIUM SULFATE ANHYDROUS 8 [hp_X]/1 mL; NAJA NAJA WHOLE 12 [hp_X]/1 mL
INACTIVE INGREDIENTS: ALCOHOL; WATER

AM-2

NDC 58264-0341-1

INDICATIONS

PURPOSE

Regulates energy flow through the heart meridian.

INGREDIENTS

ACTIVE

Colchicum autumnale 12x, Natrum sulphuricum 8x, Naja tripudians 12x

INACTIVE

20% alcohol in purified water.

SUGGESTED DOSAGE

5 to 10 drops twice a day, meridian energy excess 1 to 5 drops t.i.d, meridian lacking in energy 10 to 20 drops t.i.d.

STORAGE AND HANDLING

SHAKE WELL

Warnings

- Use only if cap seal is unbroken.

PREGNANCY OR BREAST FEEDING

- If pregnant or breastfeeding, ask a healthcare professional before use.

KEEP OUT OF REACH OF CHILDREN

- Keep this and all medication out of the reach of children.

To be used according to standard homeopathic indications.

PRINCIPAL DISPLAY PANEL - 1 FL. OZ. Bottle Label

DYNAMIC
NUTRITIONAL
ASSOCIATES, INC.

AM-2
HEART

ACUPUNCTURE MERIDIAN

1 FL. OZ.